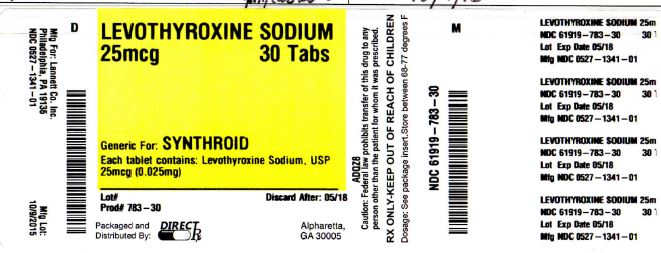 DRUG LABEL: LEVOTHYROXINE SODIUM
NDC: 61919-783 | Form: TABLET
Manufacturer: DirectRX
Category: prescription | Type: HUMAN PRESCRIPTION DRUG LABEL
Date: 20151202

ACTIVE INGREDIENTS: LEVOTHYROXINE SODIUM 0.025 mg/1 1
INACTIVE INGREDIENTS: ALUMINUM OXIDE; LACTOSE; MAGNESIUM STEARATE; CELLULOSE, MICROCRYSTALLINE; STARCH, CORN; ACACIA; FD&C YELLOW NO. 6; SILICON DIOXIDE; SODIUM STARCH GLYCOLATE TYPE A POTATO

LEVOTHYROXINE SODIUM